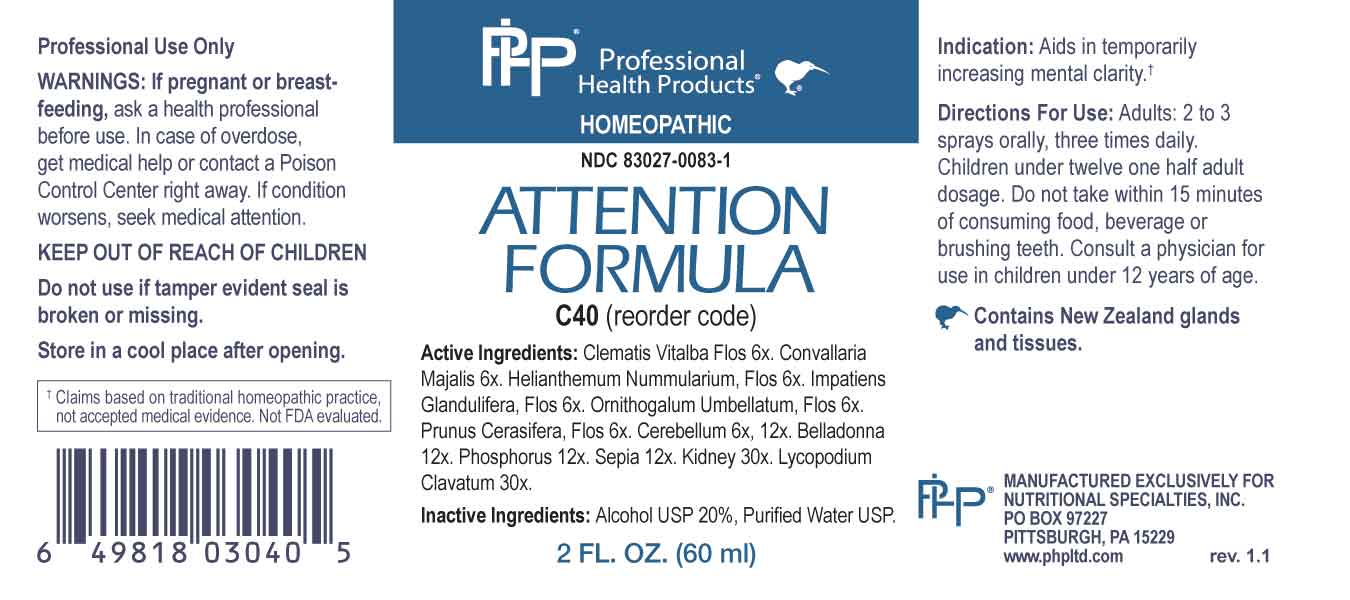 DRUG LABEL: Attention Formula
NDC: 83027-0083 | Form: SPRAY
Manufacturer: Nutritional Specialties, Inc.
Category: homeopathic | Type: HUMAN OTC DRUG LABEL
Date: 20230724

ACTIVE INGREDIENTS: CLEMATIS VITALBA FLOWER 6 [hp_X]/1 mL; CONVALLARIA MAJALIS 6 [hp_X]/1 mL; HELIANTHEMUM NUMMULARIUM FLOWER 6 [hp_X]/1 mL; IMPATIENS GLANDULIFERA FLOWER 6 [hp_X]/1 mL; ORNITHOGALUM UMBELLATUM FLOWERING TOP 6 [hp_X]/1 mL; PRUNUS CERASIFERA FLOWER 6 [hp_X]/1 mL; SUS SCROFA CEREBELLUM 6 [hp_X]/1 mL; ATROPA BELLADONNA 12 [hp_X]/1 mL; PHOSPHORUS 12 [hp_X]/1 mL; SEPIA OFFICINALIS JUICE 12 [hp_X]/1 mL; BEEF KIDNEY 30 [hp_X]/1 mL; LYCOPODIUM CLAVATUM SPORE 30 [hp_X]/1 mL
INACTIVE INGREDIENTS: WATER; ALCOHOL

DRUG FACTS:

ACTIVE INGREDIENTS:

Clematis Vitalba, Flos 6X, Convallaria Majalis 6X, Helianthemum Nummularium, Flos 6X, Impatiens Glandulifera, Flos 6X, Ornithogalum Umbellatum, Flos 6X, Prunus Cerasifera, Flos 6X, Cerebellum 6X, 12X, Belladonna 12X, Phosphorus 12X, Sepia 12X, Kidney 30X, Lycopodium Clavatum 30X.

PURPOSE:

Aids in temporary increasing mental clarity.†

†Claims based on traditional homeopathic practice, not accepted medical evidence. Not FDA evaluated.

WARNINGS:

Professional Use Only

If pregnant or breast-feeding, ask a health professional before use.

In case of overdose, get medical help or contact a Poison Control Center right away.

If condition worsens, seek medical attention.

KEEP OUT OF REACH OF CHILDREN

Do not use if tamper evident seal is broken or missing.

Store in a cool place after opening

KEEP OUT OF REACH OF CHILDREN:

In case of overdose, get medical help or contact a Poison Control Center right away.

DIRECTIONS:

Adults: 2 to 3 sprays orally, three times daily. Children under twelve one half adult dosage. Do not take within 15 minutes of consuming food, beverage or brushing teeth. Consult a physician for use in children under 12 years of age.

INDICATIONS:

Aids in temporary increasing mental clarity.†

†Claims based on traditional homeopathic practice, not accepted medical evidence. Not FDA evaluated.

INACTIVE INGREDIENTS:

Alcohol USP 20%, Purified Water USP.

QUESTIONS:

MANUFACTURED EXCLUSIVELY FOR

NUTRITIONAL SPECIALTIES, INC.

PO BOX 97227

PITTSBURG, PA 15229

www.phpltd.com

PACKAGE LABEL DISPLAY:

Professional

Health Products

HOMEOPATHIC

NDC 83027-0083-1

ATTENTION

FORMULA

2 FL. OZ (60 ml)